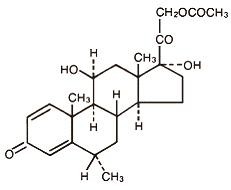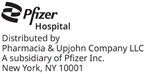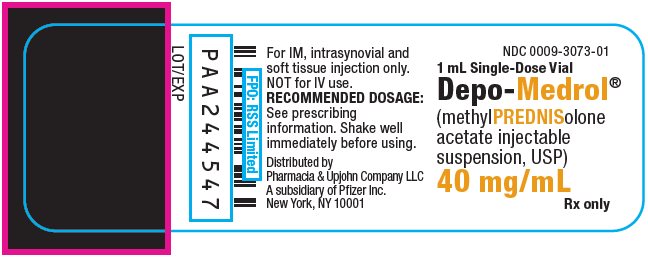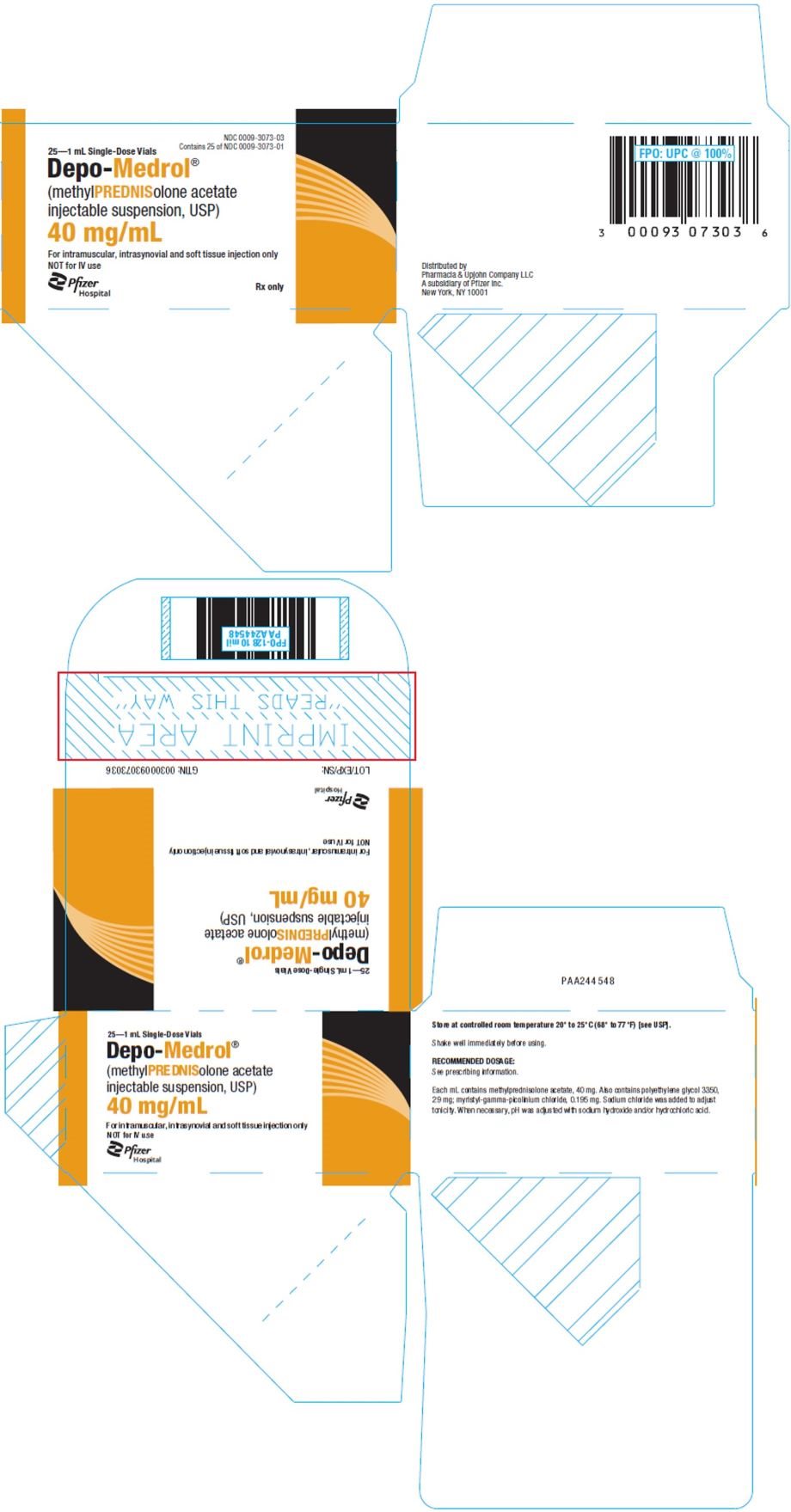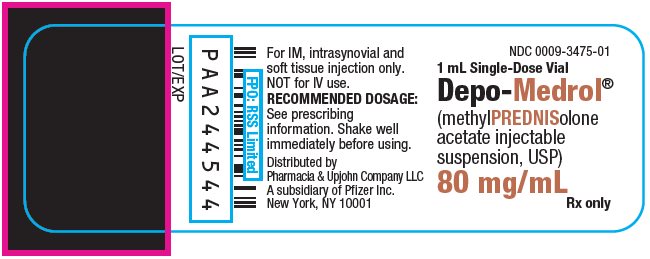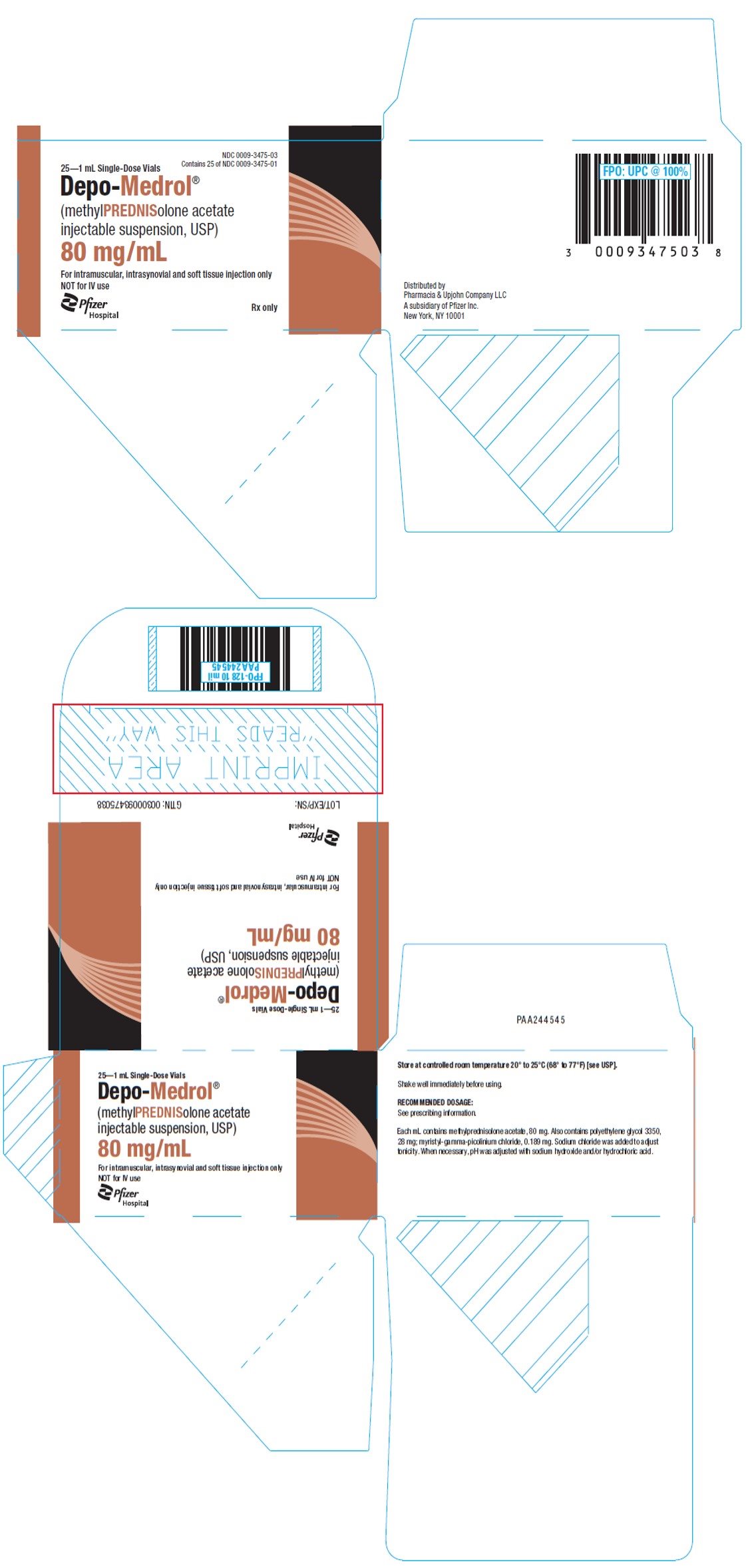 DRUG LABEL: Depo-Medrol
NDC: 0009-3073 | Form: INJECTION, SUSPENSION
Manufacturer: Pharmacia & Upjohn Company LLC
Category: prescription | Type: HUMAN PRESCRIPTION DRUG LABEL
Date: 20260121

ACTIVE INGREDIENTS: METHYLPREDNISOLONE ACETATE 40 mg/1 mL
INACTIVE INGREDIENTS: POLYETHYLENE GLYCOL 3350 29 mg/1 mL; SODIUM CHLORIDE; SODIUM HYDROXIDE; HYDROCHLORIC ACID

DEPO-MEDROL®
(methylprednisolone acetate injectable suspension, USP)

DESCRIPTION

DEPO-MEDROL is an anti-inflammatory glucocorticoid for intramuscular, intra-articular, soft tissue or intralesional injection. It is available as single-dose vials in two strengths: 40 mg/mL, 80 mg/mL.

Each mL of these preparations contains:

Methylprednisolone acetate | 40 mg | 80 mg
Polyethylene glycol 3350 | 29 mg | 28 mg
Myristyl-gamma-picolinium chloride | 0.195 mg | 0.189 mg

Sodium Chloride was added to adjust tonicity.

When necessary, pH was adjusted with sodium hydroxide and/or hydrochloric acid.

The pH of the finished product remains within the USP specified range (e.g., 3.0 to 7.0).

The chemical name for methylprednisolone acetate is pregna-1,4-diene-3,20-dione, 21-(acetyloxy)-11,17-dihydroxy-6-methyl-,(6α,11β)- and the molecular weight is 416.51. The structural formula is represented below:

DEPO-MEDROL Sterile Aqueous Suspension contains methylprednisolone acetate which is the 6-methyl derivative of prednisolone. Methylprednisolone acetate is a white or practically white, odorless, crystalline powder which melts at about 215° with some decomposition. It is soluble in dioxane, sparingly soluble in acetone, alcohol, chloroform, and methanol, and slightly soluble in ether. It is practically insoluble in water.

CLINICAL PHARMACOLOGY

Glucocorticoids, naturally occurring and synthetic, are adrenocortical steroids.

Naturally occurring glucocorticoids (hydrocortisone and cortisone), which also have salt retaining properties, are used in replacement therapy in adrenocortical deficiency states. Their synthetic analogs are used primarily for their anti-inflammatory effects in disorders of many organ systems.

INDICATIONS AND USAGE

A. For Intramuscular Administration

When oral therapy is not feasible and the strength, dosage form, and route of administration of the drug reasonably lend the preparation to the treatment of the condition, the intramuscular use of DEPO-MEDROL Sterile Aqueous Suspension is indicated as follows:

Allergic States: Control of severe or incapacitating allergic conditions intractable to adequate trials of conventional treatment in asthma, atopic dermatitis, contact dermatitis, drug hypersensitivity reactions, serum sickness, transfusion reactions.

Dermatologic Diseases: Bullous dermatitis herpetiformis, exfoliative dermatitis, mycosis fungoides, pemphigus, severe erythema multiforme (Stevens-Johnson syndrome).

Endocrine Disorders: Primary or secondary adrenocortical insufficiency (hydrocortisone or cortisone is the drug of choice; synthetic analogs may be used in conjunction with mineralocorticoids where applicable; in infancy, mineralocorticoid supplementation is of particular importance), congenital adrenal hyperplasia, hypercalcemia associated with cancer, nonsupportive thyroiditis.

Gastrointestinal Diseases: To tide the patient over a critical period of the disease in regional enteritis (systemic therapy) and ulcerative colitis.

Hematologic Disorders: Acquired (autoimmune) hemolytic anemia, congenital (erythroid) hypoplastic anemia (Diamond Blackfan anemia), pure red cell aplasia, select cases of secondary thrombocytopenia.

Miscellaneous: Trichinosis with neurologic or myocardial involvement, tuberculous meningitis with subarachnoid block or impending block when used concurrently with appropriate antituberculous chemotherapy.

Neoplastic Diseases: For palliative management of leukemias and lymphomas.

Nervous System: Cerebral edema associated with primary or metastatic brain tumor or craniotomy.

Ophthalmic Diseases: Sympathetic opthalmia, temporal arteritis, uveitis, ocular inflammatory conditions unresponsive to topical corticosteroids.

Renal Diseases: To induce diuresis or remission of proteinuria in idiopathic nephrotic syndrome, or that due to lupus erythematosus.

Respiratory Diseases: Berylliosis, fulminating or disseminated pulmonary tuberculosis when used concurrently with appropriate antituberculous chemotherapy, idiopathic eosinophilic pneumonias, symptomatic sarcoidosis.

Rheumatic Disorders: As adjunctive therapy for short-term administration (to tide the patient over an acute episode or exacerbation) in acute gouty arthritis; acute rheumatic carditis; ankylosing spondylitis; psoriatic arthritis; rheumatoid arthritis, including juvenile rheumatoid arthritis (selected cases may require low-dose maintenance therapy). For the treatment of dermatomyositis, polymyositis, and systemic lupus erythematosus.

B. For Intra-articular Or Soft Tissue Administration

(see WARNINGS)

DEPO-MEDROL is indicated as adjunctive therapy for short-term administration (to tide the patient over an acute episode or exacerbation) in acute gouty arthritis, acute and subacute bursitis, acute nonspecific tenosynovitis, epicondylitis, rheumatoid arthritis, synovitis of osteoarthritis.

C. For Intralesional Administration

DEPO-MEDROL is indicated for intralesional use in alopecia areata, discoid lupus erythematosus; keloids, localized hypertrophic, infiltrated inflammatory lesions of granuloma annulare, lichen planus, lichen simplex chronicus (neurodermatitis) and psoriatic plaques; necrobiosis lipoidica diabeticorum.

DEPO-MEDROL also may be useful in cystic tumors of an aponeurosis or tendon (ganglia).

CONTRAINDICATIONS

DEPO-MEDROL is contraindicated in patients with known hypersensitivity to the product and its constituents.

Intramuscular corticosteroid preparations are contraindicated for idiopathic thrombocytopenic purpura.

DEPO-MEDROL is contraindicated for intrathecal administration. This formulation of methylprednisolone acetate has been associated with reports of severe medical events when administered by this route.

DEPO-MEDROL is contraindicated in systemic fungal infections, except when administered as an intra-articular injection for localized joint conditions (see WARNINGS: Immunosuppression and Increased Risk of Infection, Fungal Infections).

WARNINGS

Serious Neurologic Adverse Reactions with Epidural Administration

Serious neurologic events, some resulting in death, have been reported with epidural injection of corticosteroids. Specific events reported include, but are not limited to, spinal cord infarction, paraplegia, quadriplegia, cortical blindness, and stroke. These serious neurologic events have been reported with and without use of fluoroscopy. The safety and effectiveness of epidural administration of corticosteroids have not been established, and corticosteroids are not approved for this use.

General

This product is not suitable for multi-dose use. Following administration of the desired dose, any remaining suspension should be discarded.

Injection of DEPO-MEDROL may result in dermal and/or subdermal changes forming depressions in the skin at the injection site.

In order to minimize the incidence of dermal and subdermal atrophy, care must be exercised not to exceed recommended doses in injections. Multiple small injections into the area of the lesion should be made whenever possible. The technique of intra-articular and intramuscular injection should include precautions against injection or leakage into the dermis. Injection into the deltoid muscle should be avoided because of a high incidence of subcutaneous atrophy.

It is critical that, during administration of DEPO-MEDROL, appropriate technique be used and care taken to ensure proper placement of drug.

Rare instances of anaphylactoid reactions have occurred in patients receiving corticosteroid therapy (see ADVERSE REACTIONS).

Increased dosage of rapidly acting corticosteroids is indicated in patients on corticosteroid therapy subjected to any unusual stress before, during, and after the stressful situation.

Results from one multicenter, randomized, placebo-controlled study with methylprednisolone hemisuccinate, an IV corticosteroid, showed an increase in early (at 2 weeks) and late (at 6 months) mortality in patients with cranial trauma who were determined not to have other clear indications for corticosteroid treatment. High doses of systemic corticosteroids, including DEPO-MEDROL, should not be used for the treatment of traumatic brain injury.

Cardio-renal

Average and large doses of corticosteroids can cause elevation of blood pressure, salt and water retention, and increased excretion of potassium. These effects are less likely to occur with synthetic derivatives when used in large doses. Dietary salt restriction and potassium supplementation may be necessary. All corticosteroids increase calcium excretion.

Literature reports suggest an apparent association between use of corticosteroids and left ventricular free wall rupture after a recent myocardial infarction; therefore, therapy with corticosteroids should be used with great caution in these patients.

There have been cases reported in which concomitant use of amphotericin B and hydrocortisone was followed by cardiac enlargement and congestive heart failure (see CONTRAINDICATIONS and PRECAUTIONS: Drug Interactions, Amphotericin B injection and potassium-depleting agents).

Endocrine

Hypothalamic-pituitary adrenal (HPA) axis suppression. Cushing's syndrome, and Hyperglycemia: monitor patients for these conditions with chronic use.

Corticosteroids can produce reversible HPA axis suppression with the potential for glucocorticosteroid insufficiency after withdrawal of treatment. Drug induced secondary adrenocortical insufficiency may be minimized by gradual reduction of dosage. This type of relative insufficiency may persist for months after discontinuation of therapy; therefore, in any situation of stress occurring during that period, hormone therapy should be reinstituted.

Immunosuppression and Increased Risk of Infection

Corticosteroids, including DEPO-MEDROL, suppress the immune system and increase the risk of infection with any pathogen, including viral, bacterial, fungal, protozoan, or helminthic pathogens. Corticosteroids can:

- Reduce resistance to new infections
- Exacerbate existing infections
- Increase the risk of disseminated infections
- Increase the risk of reactivation or exacerbation of latent infections
- Mask some signs of infection

Corticosteroid-associated infections can be mild but can be severe and at times fatal. The rate of infectious complications increases with increasing corticosteroid dosages.

Monitor for the development of infection and consider DEPO-MEDROL withdrawal or dosage reduction as needed.

Do not administer DEPO-MEDROL by an intraarticular, intrabursal, intratendinous or intralesional route in the presence of acute local infection.

Tuberculosis:

If DEPO-MEDROL is used to treat a condition in patients with latent tuberculosis or tuberculin reactivity, as reactivation of the disease may occur. Closely monitor such patients for reactivation. During prolonged DEPO-MEDROL therapy, patients with latent tuberculosis or tuberculin reactivity should receive chemoprophylaxis.

Varicella Zoster and Measles Viral Infections:

Varicella and measles can have a serious or even fatal course in non-immune patients taking corticosteroids, including DEPO-MEDROL. In corticosteroid‑treated patients who have not had these diseases or are non-immune, particular care should be taken to avoid exposure to varicella and measles:

- If a DEPO-MEDROL-treated patient is exposed to varicella, prophylaxis with varicella zoster immune globulin (VZIG) may be indicated. If varicella develops, treatment with antiviral agents may be considered.
- If a DEPO-MEDROL-treated patient is exposed to measles, prophylaxis with immunoglobulin (IG) may be indicated.

Hepatitis B virus reactivation can occur in patients who are hepatitis B carriers treated with immunosuppressive dosages of corticosteroids, including DEPO‑MEDROL. Reactivation can also occur infrequently in corticosteroid‑treated patients who appear to have resolved hepatitis B infection.

Screen patients for hepatitis B infection before initiating immunosuppressive (e.g., prolonged) treatment with DEPO-MEDROL. For patients who show evidence of hepatitis B infection, recommend consultation with physicians with expertise in managing hepatitis B regarding monitoring and consideration for hepatitis B antiviral therapy.

Fungal Infections:

Corticosteroids, including DEPO-MEDROL, may exacerbate systemic fungal infections; therefore, avoid DEPO-MEDROL use in the presence of such infections unless DEPO-MEDROL is needed to control drug reactions. For patients on chronic DEPO-MEDROL therapy who develop systemic fungal infections, DEPO-MEDROL withdrawal or dosage reduction is recommended.

Amebiasis:

Corticosteroids, including DEPO-MEDROL, may activate latent amebiasis. Therefore, it is recommended that latent amebiasis or active amebiasis be ruled out before initiating DEPO-MEDROL in patients who have spent time in the tropics or patients with unexplained diarrhea.

Strongyloides Infestation:

Corticosteroids, including DEPO-MEDROL, should be used with great care in patients with known or suspected Strongyloides (threadworm) infestation. In such patients, corticosteroid-induced immunosuppression may lead to Strongyloides hyperinfection and dissemination with widespread larval migration, often accompanied by severe enterocolitis and potentially fatal gram-negative septicemia.

Cerebral Malaria:

Avoid corticosteroids, including DEPO-MEDROL, in patients with cerebral malaria.

Vaccinations

Administration of live or live, attenuated vaccines is contraindicated in patients receiving immunosuppressive doses of corticosteroids. Killed or inactivated vaccines may be administered. However, the response to such vaccines cannot be predicted.

Immunization procedures may be undertaken in patients who are receiving corticosteroids as replacement therapy (e.g., for Addison’s disease).

Ophthalmic

Use of corticosteroids may produce posterior subcapsular cataracts, glaucoma with possible damage to the optic nerves, and may enhance the establishment of secondary ocular infections due to bacteria, fungi, or viruses. The use of systemic corticosteroids is not recommended in the treatment of optic neuritis and may lead to an increase in the risk of new episodes. Corticosteroids should be used cautiously in patients with ocular herpes simplex because of corneal perforation. Corticosteroids should not be used in active ocular herpes simplex.

Kaposi’s sarcoma has been reported to occur in patients receiving corticosteroid therapy, most often for chronic conditions. Discontinuation of corticosteroids may result in clinical improvement of Kaposi’s sarcoma.

PRECAUTIONS

General

This product, like many other corticosteroids, is sensitive to heat. Therefore, it should not be autoclaved when it is desirable to sterilize the exterior of the vial.

The lowest possible dose of corticosteroid should be used to control the condition under treatment. When reduction in dosage is possible, the reduction should be gradual.

Since complications of treatment with glucocorticosteroids are dependent on the size of the dose and the duration of treatment, a risk/benefit decision must be made in each individual case as to dose and duration of treatment and as to whether daily or intermittent therapy should be used.

Cardio-renal

Caution is required in patients with systemic sclerosis because an increased incidence of scleroderma renal crisis has been observed with corticosteroids, including methylprednisolone.

As sodium retention with resultant edema and potassium loss may occur in patients receiving corticosteroids, these agents should be used with caution in patients with congestive heart failure or renal insufficiency.

Endocrine

Drug-induced secondary adrenocortical insufficiency may be minimized by gradual reduction of dosage. This type of relative insufficiency may persist for months after discontinuation of therapy; therefore, in any situation of stress occurring during that period, hormone therapy should be reinstituted.

Metabolic clearance of corticosteroids is decreased in hypothyroid patients and increased in hyperthyroid patients. Changes in thyroid status of the patient may necessitate adjustment in dosage.

Gastrointestinal

Steroids should be used with caution in active or latent peptic ulcers, diverticulitis, fresh intestinal anastomoses, and nonspecific ulcerative colitis, since they may increase the risk of perforation.

Signs of peritoneal irritation following gastrointestinal perforation in patients receiving corticosteroids may be minimal or absent.

There is an enhanced effect due to decreased metabolism of corticosteroids in patients with cirrhosis.

Parenteral Administration

Intra-articularly injected corticosteroids may be systemically absorbed.

Appropriate examination of any joint fluid present is necessary to exclude a septic process.

A marked increase in pain accompanied by local swelling, further restriction of joint motion, fever, and malaise are suggestive of septic arthritis. If this complication occurs and diagnosis of sepsis is confirmed, appropriate antimicrobial therapy should be instituted.

Injection of a steroid into an infected site is to be avoided. Local injection of a steroid into a previously infected joint is not usually recommended.

Musculoskeletal

Corticosteroids decrease bone formation and increase bone resorption both through their effect on calcium regulation (e.g., decreasing absorption and increasing excretion) and inhibition of osteoblast function. This, together with a decrease in the protein matrix of the bone secondary to an increase in protein catabolism, and reduced sex hormone production, may lead to an inhibition of bone growth in pediatric patients and the development of osteoporosis at any age. Special consideration should be given to patients at increased risk of osteoporosis (i.e., postmenopausal women) before initiating corticosteroid therapy.

Neuro-psychiatric

An acute myopathy has been observed with the use of high doses of corticosteroids, most often occurring in patients with disorders of neuromuscular transmission (e.g., myasthenia gravis), or in patients receiving concomitant therapy with neuromuscular blocking drugs (e.g., pancuronium). This acute myopathy is generalized, may involve ocular and respiratory muscles, and may result in quadriparesis. Elevation of creatine kinase may occur. Clinical improvement or recovery after stopping corticosteroids may require weeks to years.

Psychic derangements may appear when corticosteroids are used, ranging from euphoria, insomnia, mood swings, personality changes, and severe depression to frank psychotic manifestations. Also, existing emotional instability or psychotic tendencies may be aggravated by corticosteroids.

Ophthalmic

Intraocular pressure may become elevated in some individuals. If steroid therapy is continued long-term, intraocular pressure should be monitored.

Corticosteroids should be used cautiously in patients with ocular herpes simplex for fear of corneal perforation.

Tumor Lysis Syndrome

In post marketing experience, tumor lysis syndrome (TLS) has been reported in patients with malignancies, including hematological malignancies and solid tumors, following the use of systemic corticosteroids alone or in combination with other chemotherapeutic agents. Patients at high risk of TLS, such as patients with tumors that have a high proliferative rate, high tumor burden and high sensitivity to cytotoxic agents, should be monitored closely and appropriate precautions should be taken.

Information for Patients

Patients should be warned not to discontinue the use of corticosteroids abruptly or without medical supervision, to advise any medical attendants that they are taking corticosteroids and to seek medical advice at once should they develop a fever or other signs of infection.

Persons who are on corticosteroids should be warned to avoid exposure to chicken pox or measles. Patients should also be advised that if they are exposed, medical advice should be sought without delay.

Drug Interactions

Aminoglutethimide: Aminoglutethimide may lead to a loss of corticosteroid-induced adrenal suppression.

Amphotericin B injection and potassium-depleting agents: When corticosteroids are administered concomitantly with potassium depleting agents (e.g., amphotericin B, diuretics), patients should be observed closely for development of hypokalemia. There have been cases reported in which concomitant use of amphotericin B and hydrocortisone was followed by cardiac enlargement and congestive heart failure.

Antibiotics: Macrolide antibiotics have been reported to cause a significant decrease in corticosteroid clearance (see PRECAUTIONS: Drug Interactions, Hepatic Enzyme Inhibitors).

Anticholinesterases: Concomitant use of anticholinesterase agents and corticosteroids may produce severe weakness in patients with myasthenia gravis. If possible, anticholinesterase agents should be withdrawn at least 24 hours before initiating corticosteroid therapy.

Anticoagulants, oral: Coadministration of corticosteroids and warfarin usually results in inhibition of response to warfarin, although there have been some conflicting reports. Therefore, coagulation indices should be monitored frequently to maintain the desired anticoagulant effect.

Antidiabetics: Because corticosteroids may increase blood glucose concentration, dosage adjustments of antidiabetic agents may be required.

Antitubercular drugs: Serum concentrations of isoniazid may be decreased.

Cholestyramine: Cholestyramine may increase the clearance of oral corticosteroids.

Cyclosporine: Increased activity of both cyclosporine and corticosteroids may occur when the two are used concurrently. Convulsions have been reported with this concurrent use.

Digitalis glycosides: Patients on digitalis glycosides may be at risk of arrhythmias due to hypokalemia.

Estrogens, including oral contraceptives: Estrogens may decrease the hepatic metabolism of certain corticosteroids, thereby increasing their effect.

Hepatic Enzyme Inducers (e.g., barbiturates, phenytoin, carbamazepine, rifampin): Drugs which induce cytochrome P450 3A4 enzyme activity may enhance the metabolism of corticosteroids and require that the dosage of the corticosteroid be increased.

Hepatic Enzyme Inhibitors (e.g., ketoconazole, macrolide antibiotics such as erythromycin and troleandomycin): Drugs which inhibit cytochrome P450 3A4 have the potential to result in increased plasma concentrations of corticosteroids.

Ketoconazole: Ketoconazole has been reported to significantly decrease the metabolism of certain corticosteroids by up to 60%, leading to an increased risk of corticosteroid side effects.

Nonsteroidal anti-inflammatory drugs (NSAIDs): Concomitant use of aspirin (or other nonsteroidal anti-inflammatory agents) and corticosteroids increases the risk of gastrointestinal side effects. Aspirin should be used cautiously in conjunction with corticosteroids in hypoprothrombinemia. The clearance of salicylates may be increased with concurrent use of corticosteroids.

Skin tests: Corticosteroids may suppress reactions to skin tests.

Vaccines: Patients on prolonged corticosteroid therapy may exhibit a diminished response to toxoids and live or inactivated vaccines due to inhibition of antibody response. Corticosteroids may also potentiate the replication of some organisms contained in live attenuated vaccines. Routine administration of vaccines or toxoids should be deferred until corticosteroid therapy is discontinued if possible (see WARNINGS: Immunosuppression and Increased Risk of Infection, Vaccinations).

Carcinogenesis, Mutagenesis, Impairment of Fertility

No adequate studies have been conducted in animals to determine whether corticosteroids have a potential for carcinogenesis or mutagenesis.

Steroids may increase or decrease motility and number of spermatozoa in some patients.

Corticosteroids have been shown to impair fertility in male rats.

Pregnancy:

Teratogenic Effects

Corticosteroids have been shown to be teratogenic in many species when given in doses equivalent to the human dose. Animal studies in which corticosteroids have been given to pregnant mice, rats, and rabbits have yielded an increased incidence of cleft palate in the offspring. There are no adequate and well-controlled studies in pregnant women. Corticosteroids should be used during pregnancy only if the potential benefit justifies the potential risk to the fetus. Infants born to mothers who have received corticosteroids during pregnancy should be carefully observed for signs of hypoadrenalism.

Nursing Mothers

Systemically administered corticosteroids appear in human milk and could suppress growth, interfere with endogenous corticosteroid production, or cause other untoward effects. Because of the potential for serious adverse reactions in nursing infants from corticosteroids, a decision should be made whether to discontinue nursing or discontinue the drug, taking into account the importance of the drug to the mother.

Pediatric Use

The efficacy and safety of corticosteroids in the pediatric population are based on the well-established course of effect of corticosteroids which is similar in pediatric and adult populations. Published studies provide evidence of efficacy and safety in pediatric patients for the treatment of nephritic syndrome (patients >2 years of age) and aggressive lymphomas and leukemias (patients >1 month of age). Other indications for pediatric use of corticosteroids (e.g., severe asthma and wheezing) are based on adequate and well-controlled clinical trials conducted in adults, on the premises that the course of the diseases and their pathophysiology are considered to be substantially similar in both populations.

The adverse effects of corticosteroids in pediatric patients are similar to those in adults (see ADVERSE REACTIONS). Like adults, pediatric patients should be carefully observed with frequent measurements of blood pressure, weight, height, intraocular pressure, and clinical evaluation for the presence of infection, psychosocial disturbances, thromboembolism, peptic ulcers, cataracts, and osteoporosis. Pediatric patients who are treated with corticosteroids by any route, including systemically administered corticosteroids, may experience a decrease in their growth velocity. This negative impact of corticosteroids on growth has been observed at low systemic doses and in the absence of laboratory evidence of HPA axis suppression (i.e., cosyntropin stimulation and basal cortisol plasma levels). Growth velocity may therefore be a more sensitive indicator of systemic corticosteroid exposure in pediatric patients than some commonly used tests of HPA axis function. The linear growth of pediatric patients treated with corticosteroids should be monitored, and the potential growth effects of prolonged treatment should be weighed against clinical benefits obtained and the availability of treatment alternatives. In order to minimize the potential growth effects of corticosteroids, pediatric patients should be titrated to the lowest effective dose.

Geriatric Use

Clinical studies did not include sufficient numbers of subjects aged 65 and over to determine whether they respond differently from younger subjects. Other reported clinical experience has not identified differences in responses between the elderly and younger patients. In general, dose selection for an elderly patient should be cautious, usually starting at the low end of the dosing range, reflecting the greater frequency of decreased hepatic, renal, or cardiac function, and of concomitant disease or other drug therapy.

ADVERSE REACTIONS

The following adverse reactions have been reported with DEPO-MEDROL or other corticosteroids:

Allergic reactions: Allergic or hypersensitivity reactions, anaphylactoid reaction, anaphylaxis, angioedema.

Blood and lymphatic system disorders: Leukocytosis.

Cardiovascular: Bradycardia, cardiac arrest, cardiac arrhythmias, cardiac enlargement, circulatory collapse, congestive heart failure, fat embolism, hypertension, hypertrophic cardiomyopathy in premature infants, myocardial rupture following recent myocardial infarction (see WARNINGS), pulmonary edema, syncope, tachycardia, thromboembolism, thrombophlebitis, vasculitis.

Dermatologic: Acne, allergic dermatitis, cutaneous and subcutaneous atrophy, dry scaly skin, ecchymoses and petechiae, edema, erythema, hyperpigmentation, hypopigmentation, impaired wound healing, increased sweating, rash, sterile abscess, striae, suppressed reactions to skin tests, thin fragile skin, thinning scalp hair, urticaria.

Endocrine: Decreased carbohydrate and glucose tolerance, development of cushingoid state, glycosuria, hirsutism, hypertrichosis, increased requirements for insulin or oral hypoglycemic agents in diabetes, manifestations of latent diabetes mellitus, menstrual irregularities, secondary adrenocortical and pituitary unresponsiveness (particularly in times of stress, as in trauma, surgery, or illness), suppression of growth in pediatric patients.

Fluid and electrolyte disturbances: Congestive heart failure in susceptible patients, fluid retention, hypokalemic alkalosis, potassium loss, sodium retention.

Gastrointestinal: Abdominal distention, bowel/bladder dysfunction (after intrathecal administration), elevation in serum liver enzyme levels (usually reversible upon discontinuation), hepatomegaly, increased appetite, nausea, pancreatitis, peptic ulcer with possible subsequent perforation and hemorrhage, perforation of the small and large intestine (particularly in patients with inflammatory bowel disease), ulcerative esophagitis.

Metabolic: Negative nitrogen balance due to protein catabolism.

Musculoskeletal: Aseptic necrosis of femoral and humeral heads, calcinosis (following intra-articular or intra-lesional use), Charcot-like arthropathy, loss of muscle mass, muscle weakness, osteoporosis, pathologic fracture of long bones, post injection flare (following intra-articular, soft tissue, and tendon sheath injections), steroid myopathy, tendon rupture, vertebral compression fractures.

Neurologic/Psychiatric: Convulsions, depression, emotional instability, euphoria, headache, increased intracranial pressure with papilledema (pseudotumor cerebri) usually following discontinuation of treatment, insomnia, mood swings, neuritis, neuropathy, paresthesia, personality changes, psychic disorders, vertigo.

Ophthalmic: Exophthalmoses, glaucoma, increased intraocular pressure, posterior subcapsular cataracts.

Vascular: Flushing.

Other: Abnormal fat deposits, decreased resistance to infection, hiccups, increased or decreased motility and number of spermatozoa, injection site infections following non-sterile administration (see WARNINGS), malaise, moon face, weight gain.

The following adverse reactions have been reported with the following routes of administration:

Intrathecal/Epidural: Arachnoiditis, bowel/bladder dysfunction, headache, meningitis, parapareisis/paraplegia, seizures, sensory disturbances.

Intranasal: Allergic reactions, rhinitis, temporary/permanent visual impairment including blindness.

Ophthalmic: Increased intraocular pressure, infection, ocular and periocular inflammation including allergic reactions, residue or slough at injection site, temporary/permanent visual impairment including blindness.

Miscellaneous injection sites (scalp, tonsillar fauces, sphenopalatine ganglion): Blindness.

OVERDOSAGE

Treatment of acute overdosage is by supportive and symptomatic therapy. For chronic overdosage in the face of severe disease requiring continuous steroid therapy, the dosage of the corticosteroid may be reduced only temporarily, or alternate day treatment may be introduced.

DOSAGE AND ADMINISTRATION

Because of possible physical incompatibilities, DEPO-MEDROL Sterile Aqueous Suspension should not be diluted or mixed with other solutions.

The initial dosage of parenterally administered DEPO-MEDROL will vary from 4 to 120 mg, depending on the specific disease entity being treated. However, in certain overwhelming, acute, life-threatening situations, administration in dosages exceeding the usual dosages may be justified and may be in multiples of the oral dosages.

It Should Be Emphasized that Dosage Requirements Are Variable and Must Be Individualized on the Basis of the Disease Under Treatment and the Response of the Patient. After a favorable response is noted, the proper maintenance dosage should be determined by decreasing the initial drug dosage in small decrements at appropriate time intervals until the lowest dosage which will maintain an adequate clinical response is reached. Situations which may make dosage adjustments necessary are changes in clinical status secondary to remissions or exacerbations in the disease process, the patient’s individual drug responsiveness, and the effect of patient exposure to stressful situations not directly related to the disease entity under treatment. In this latter situation, it may be necessary to increase the dosage of the corticosteroid for a period of time consistent with the patient’s condition. If after long-term therapy the drug is to be stopped, it is recommended that it be withdrawn gradually rather than abruptly.

A. Administration for Local Effect

Therapy with DEPO-MEDROL does not obviate the need for the conventional measures usually employed. Although this method of treatment will ameliorate symptoms, it is in no sense a cure and the hormone has no effect on the cause of the inflammation.

1. Rheumatoid Arthritis and Osteoarthritis:

The dose for intra-articular administration depends upon the size of the joint and varies with the severity of the condition in the individual patient. In chronic cases, injections may be repeated at intervals ranging from one to five or more weeks, depending upon the degree of relief obtained from the initial injection. The doses in the following table are given as a general guide:

Size; of Joint | Examples | Range; of Dosage
Large | Knees; Ankles; Shoulders | 20 to 80 mg
Medium | Elbows; Wrists | 10 to 40 mg
Small | Metacarpophalangeal; Interphalangeal; Sternoclavicular; Acromioclavicular | 4 to 10 mg

Procedure: It is recommended that the anatomy of the joint involved be reviewed before attempting intra-articular injection. To obtain the full anti‑inflammatory effect, it is important that the injection be made into the synovial space. Employing the same sterile technique as for a lumbar puncture, a sterile 20 to 24 gauge needle (on a dry syringe) is quickly inserted into the synovial cavity. Procaine infiltration is elective. The aspiration of only a few drops of joint fluid proves the joint space has been entered by the needle. The injection site for each joint is determined by the location where the synovial cavity is most superficial and most free of large vessels and nerves. With the needle in place, the aspirating syringe is removed and replaced by a second syringe containing the desired amount of DEPO-MEDROL. The plunger is then pulled outward slightly to aspirate synovial fluid and to make sure the needle is still in the synovial space. After injection, the joint is moved gently a few times to aid mixing of the synovial fluid and the suspension. The site is covered with a small sterile dressing.

Suitable sites for intra-articular injection are the knee, ankle, wrist, elbow, shoulder, phalangeal, and hip joints. Since difficulty is not infrequently encountered in entering the hip joint, precautions should be taken to avoid any large blood vessels in the area. Joints not suitable for injection are those that are anatomically inaccessible such as the spinal joints and those like the sacroiliac joints that are devoid of synovial space. Treatment failures are most frequently the result of failure to enter the joint space. Little or no benefit follows injection into surrounding tissue. If failures occur when injections into the synovial spaces are certain, as determined by aspiration of fluid, repeated injections are usually futile.

If a local anesthetic is used prior to injection of DEPO-MEDROL, the anesthetic package insert should be read carefully, and all the precautions observed.

2. Bursitis:

The area around the injection site is prepared in a sterile way and a wheal at the site made with 1 percent procaine hydrochloride solution. A 20 to 24 gauge needle attached to a dry syringe is inserted into the bursa and the fluid aspirated. The needle is left in place and the aspirating syringe changed for a small syringe containing the desired dose. After injection, the needle is withdrawn and a small dressing applied.

3. Miscellaneous: Ganglion, Tendinitis, Epicondylitis:

In the treatment of conditions such as tendinitis or tenosynovitis, care should be taken following application of a suitable antiseptic to the overlying skin to inject the suspension into the tendon sheath rather than into the substance of the tendon. The tendon may be readily palpated when placed on a stretch. When treating conditions such as epicondylitis, the area of greatest tenderness should be outlined carefully and the suspension infiltrated into the area. For ganglia of the tendon sheaths, the suspension is injected directly into the cyst. In many cases, a single injection causes a marked decrease in the size of the cystic tumor and may affect disappearance. The usual sterile precautions should be observed, of course, with each injection.

The dose in the treatment of the various conditions of the tendinous or bursal structures listed above varies with the condition being treated and ranges from 4 to 30 mg. In recurrent or chronic conditions, repeated injections may be necessary.

4. Injections for Local Effect in Dermatologic Conditions:

Following cleansing with an appropriate antiseptic such as 70% alcohol, 20 to 60 mg is injected into the lesion. It may be necessary to distribute doses ranging from 20 to 40 mg by repeated local injections in the case of large lesions. Care should be taken to avoid injection of sufficient material to cause blanching since this may be followed by a small slough. One to four injections are usually employed, the intervals between injections varying with the type of lesion being treated and the duration of improvement produced by the initial injection.

B. Administration for Systemic Effect

The intramuscular dosage will vary with the condition being treated. When employed as a temporary substitute for oral therapy, a single injection during each 24-hour period of a dose of the suspension equal to the total daily oral dose of MEDROL® Tablets (methylprednisolone tablets, USP) is usually sufficient. When a prolonged effect is desired, the weekly dose may be calculated by multiplying the daily oral dose by 7 and given as a single intramuscular injection.

In pediatric patients, the initial dose of methylprednisolone may vary depending on the specific disease entity being treated. Dosage must be individualized according to the severity of the disease and response of the patient. The recommended dosage may be reduced for pediatric patients, but dosage should be governed by the severity of the condition rather than by strict adherence to the ratio indicated by age or body weight.

In patients with the adrenogenital syndrome, a single intramuscular injection of 40 mg every two weeks may be adequate. For maintenance of patients with rheumatoid arthritis, the weekly intramuscular dose will vary from 40 to 120 mg. The usual dosage for patients with dermatologic lesions benefited by systemic corticoid therapy is 40 to 120 mg of methylprednisolone acetate administered intramuscularly at weekly intervals for one to four weeks. In acute severe dermatitis due to poison ivy, relief may result within 8 to 12 hours following intramuscular administration of a single dose of 80 to 120 mg. In chronic contact dermatitis, repeated injections at 5 to 10 day intervals may be necessary. In seborrheic dermatitis, a weekly dose of 80 mg may be adequate to control the condition.

Following intramuscular administration of 80 to 120 mg to asthmatic patients, relief may result within 6 to 48 hours and persist for several days to two weeks.

If signs of stress are associated with the condition being treated, the dosage of the suspension should be increased. If a rapid hormonal effect of maximum intensity is required, the intravenous administration of highly soluble methylprednisolone sodium succinate is indicated.

For the purpose of comparison, the following is the equivalent milligram dose of the various glucocorticoids:

Cortisone, 25 | Triamcinolone, 4
Hydrocortisone, 20 | Paramethasone, 2
Prednisolone, 5 | Betamethasone, 0.75
Prednisone, 5 | Dexamethasone, 0.75
Methylprednisolone, 4

These dose relationships apply only to oral or intravenous administration of these compounds. When these substances or their derivatives are injected intramuscularly or into joint spaces, their relative properties may be greatly altered.

HOW SUPPLIED

DEPO-MEDROL Sterile Aqueous Suspension is available as single-dose vials in the following strengths and package sizes:

40 mg per mL |  | 80 mg per mL
1 mL vials | NDC 0009-3073-01 | 1 mL vials | NDC 0009-3475-01
25 × 1 mL vials | NDC 0009-3073-03 | 25 × 1 mL vials | NDC 0009-3475-03

STORAGE AND HANDLING

Store at controlled room temperature 20° to 25°C (68° to 77°F) [see USP].

This product's label may have been updated. For current full prescribing information, please visit www.pfizer.com.

For medical information about DEPO-MEDROL, please visit www.pfizermedinfo.com or call 1-800-438-1985.

LAB-0160-20.0
Revised November 2025

PRINCIPAL DISPLAY PANEL - 40 mg/mL Vial Label

NDC 0009-3073-01

1 mL Single-Dose Vial
Depo-Medrol®

(methylPREDNISolone
acetate injectable
suspension, USP)

40 mg/mL

Rx only

PRINCIPAL DISPLAY PANEL - 40 mg/mL Vial Carton

NDC 0009-3073-03
Contains 25 of NDC 0009-3073-01

25—1 mL Single-Dose Vials
Depo-Medrol®

(methylPREDNISolone acetate
injectable suspension, USP)

40 mg/mL

For intramuscular, intrasynovial and soft tissue injection only
NOT for IV use

Pfizer Hospital

Rx only

PRINCIPAL DISPLAY PANEL - 80 mg/mL Vial Label

NDC 0009-3475-01

1 mL Single-Dose Vial
Depo-Medrol®

(methylPREDNISolone
acetate injectable
suspension, USP)

80 mg/mL

Rx only

PRINCIPAL DISPLAY PANEL - 80 mg/mL Vial Carton

NDC 0009-3475-03
Contains 25 of NDC 0009-3475-01

25—1 mL Single-Dose Vials
Depo-Medrol®

(methylPREDNISolone acetate
injectable suspension, USP)

80 mg/mL

For intramuscular, intrasynovial and soft tissue injection only
NOT for IV use

Pfizer Hospital

Rx only